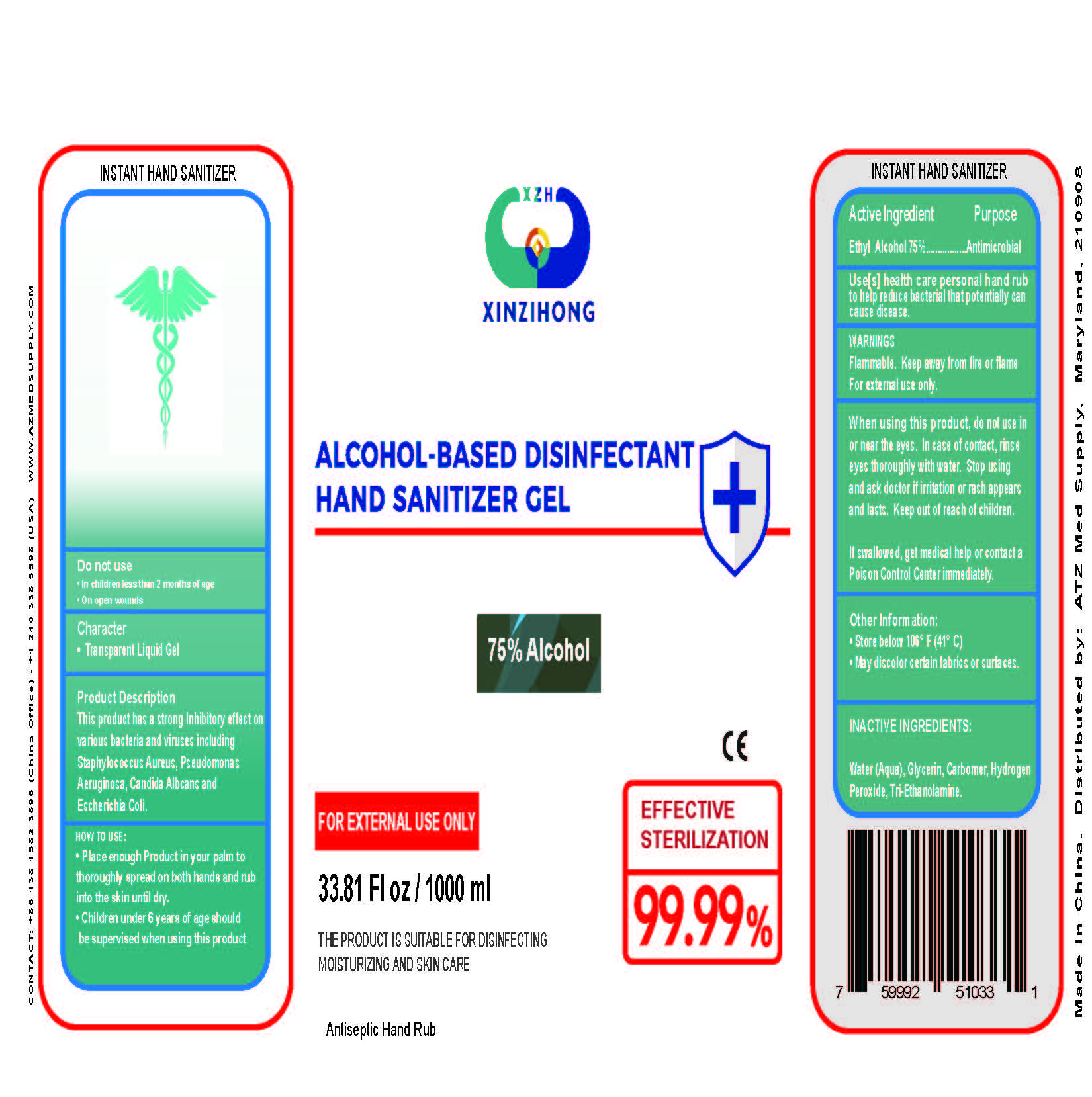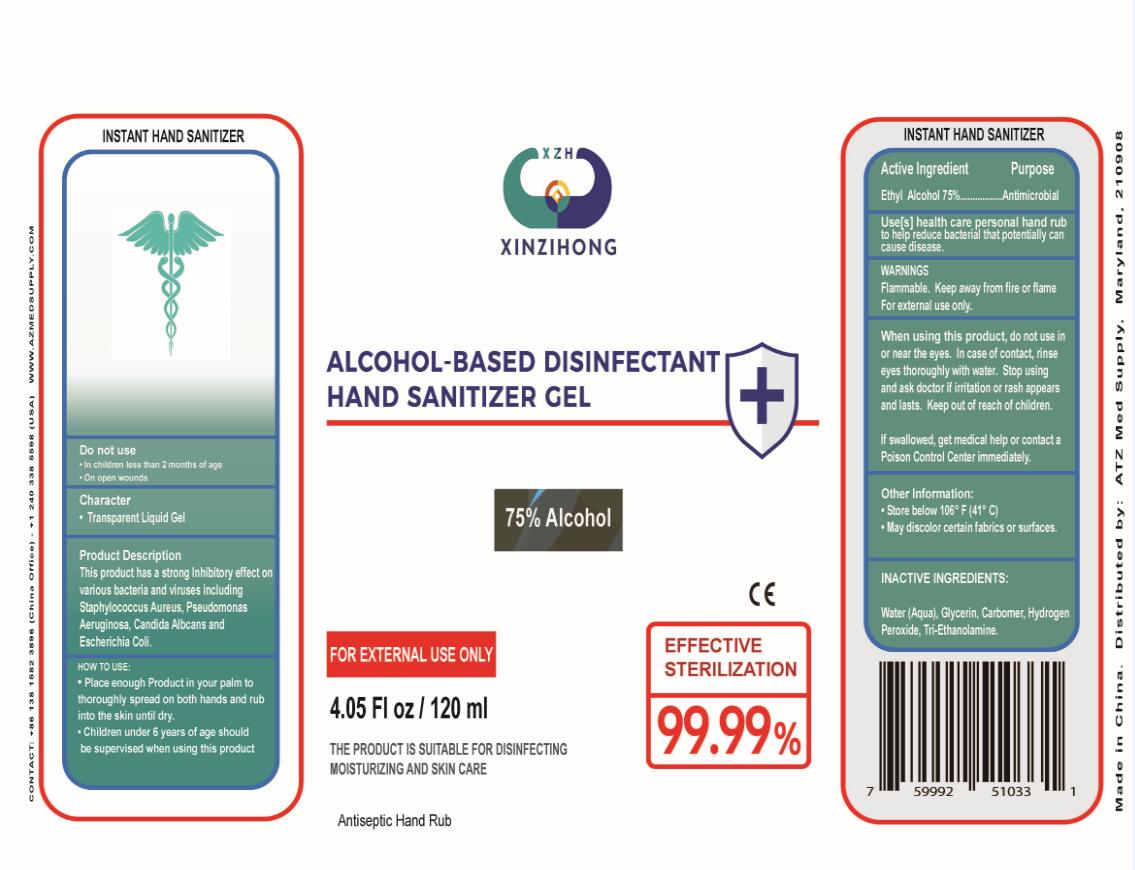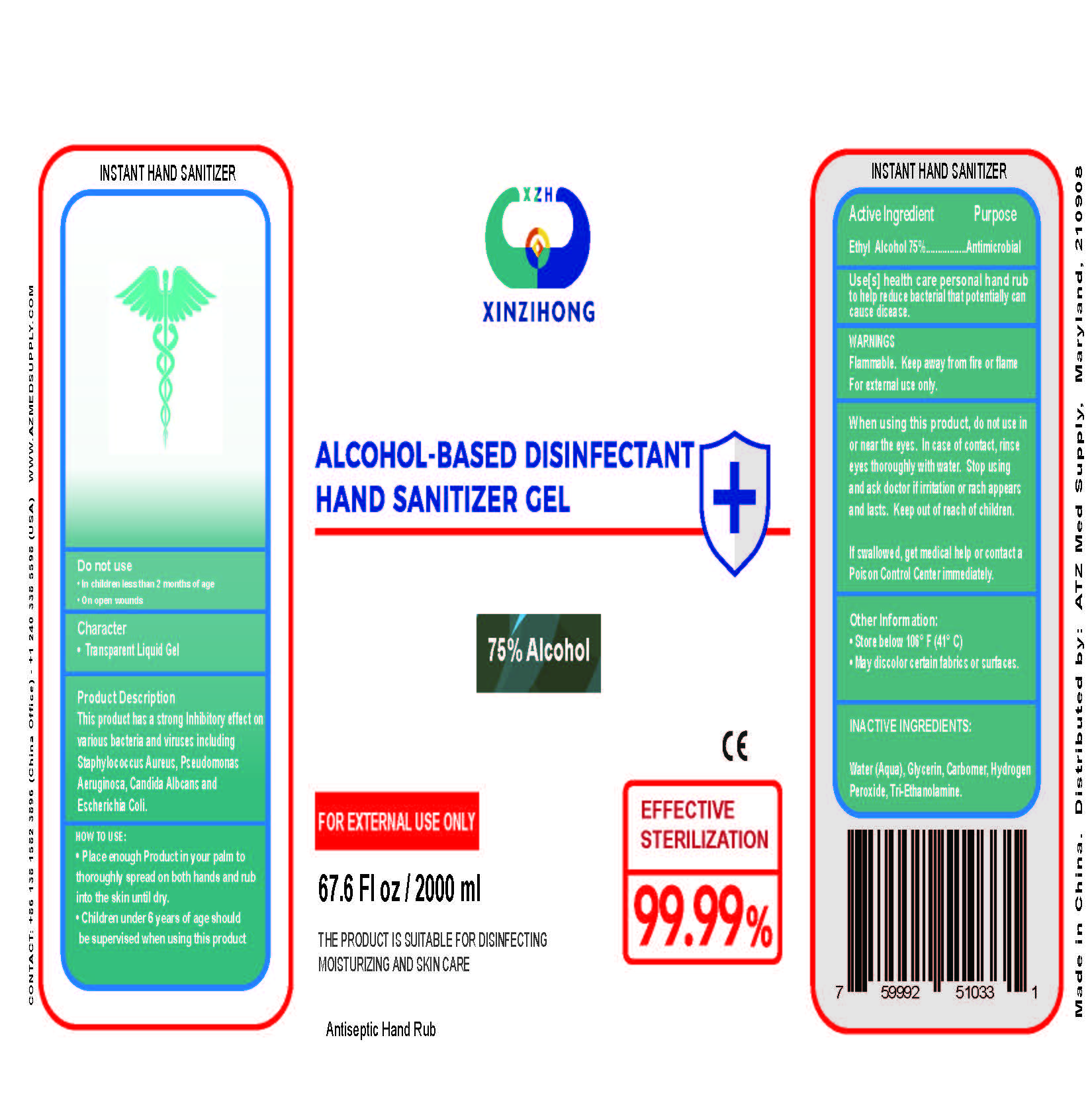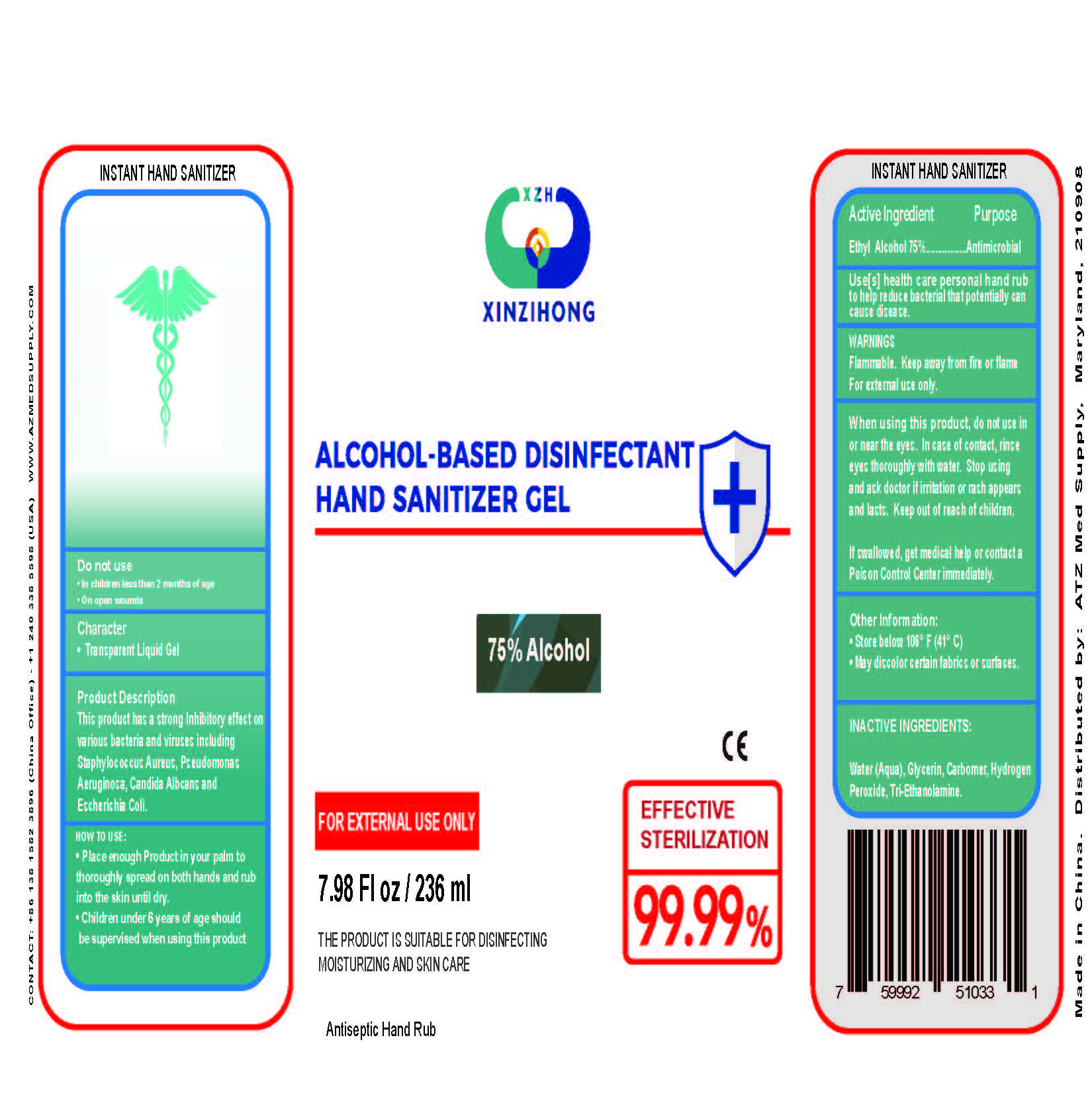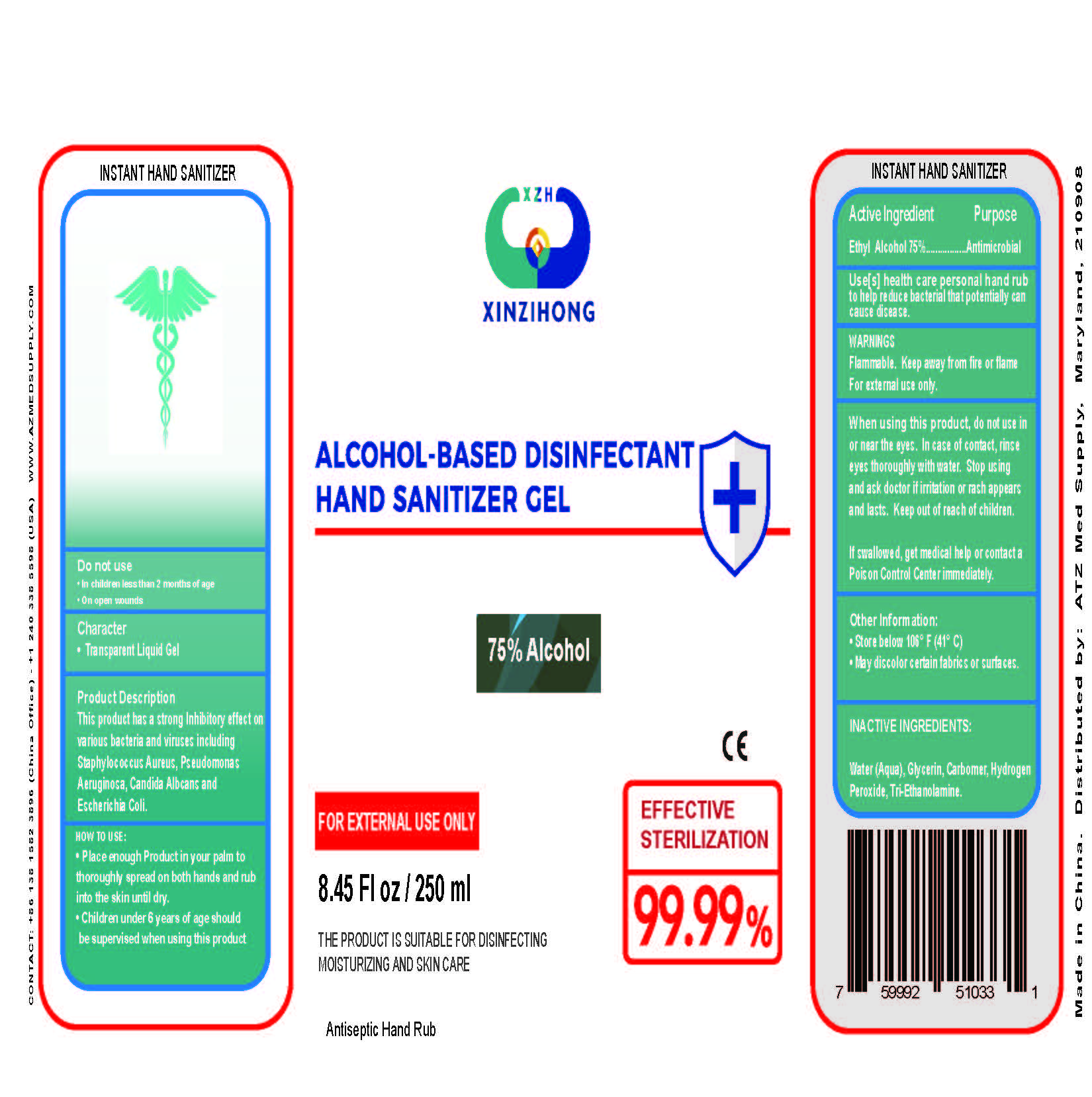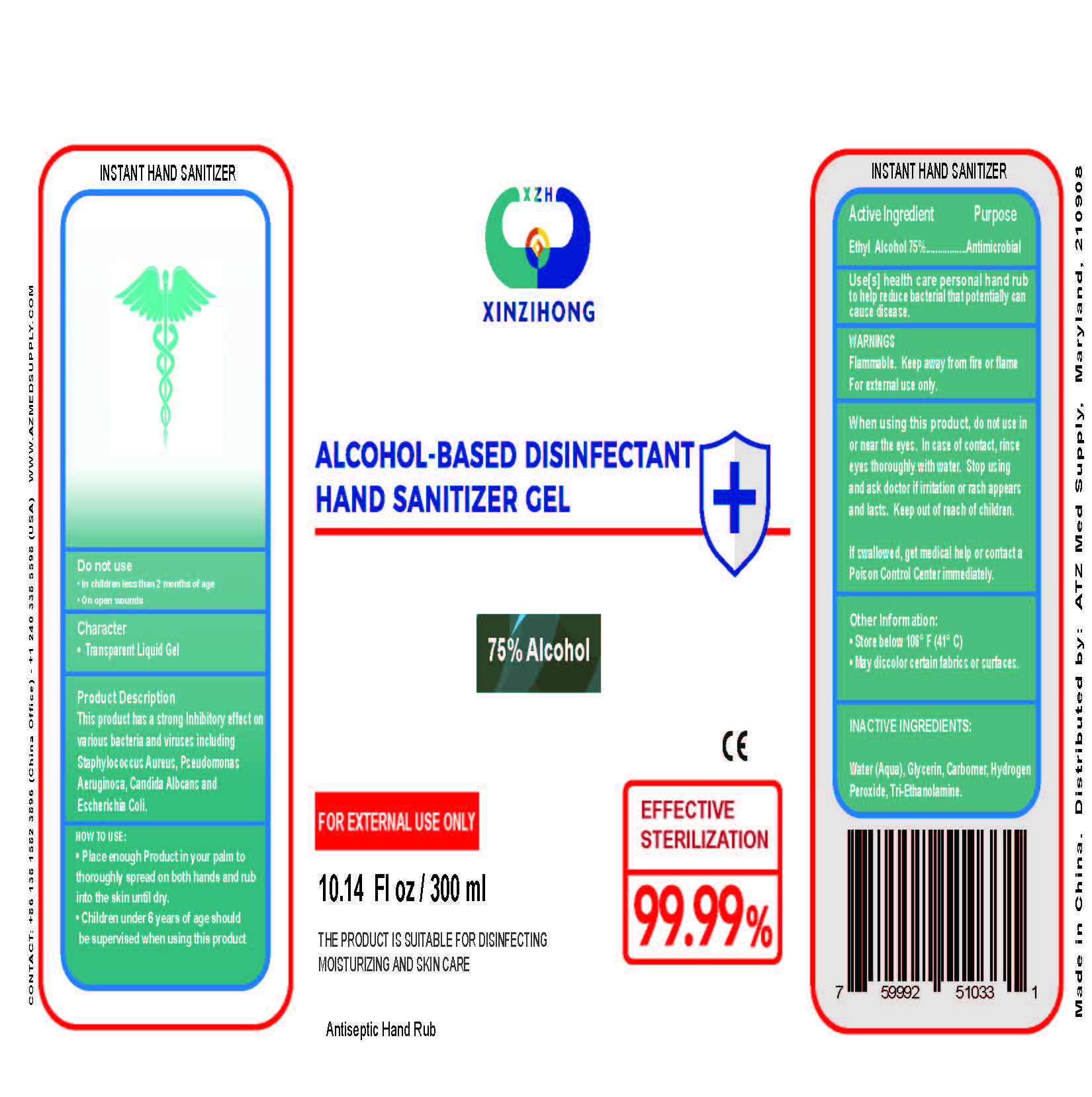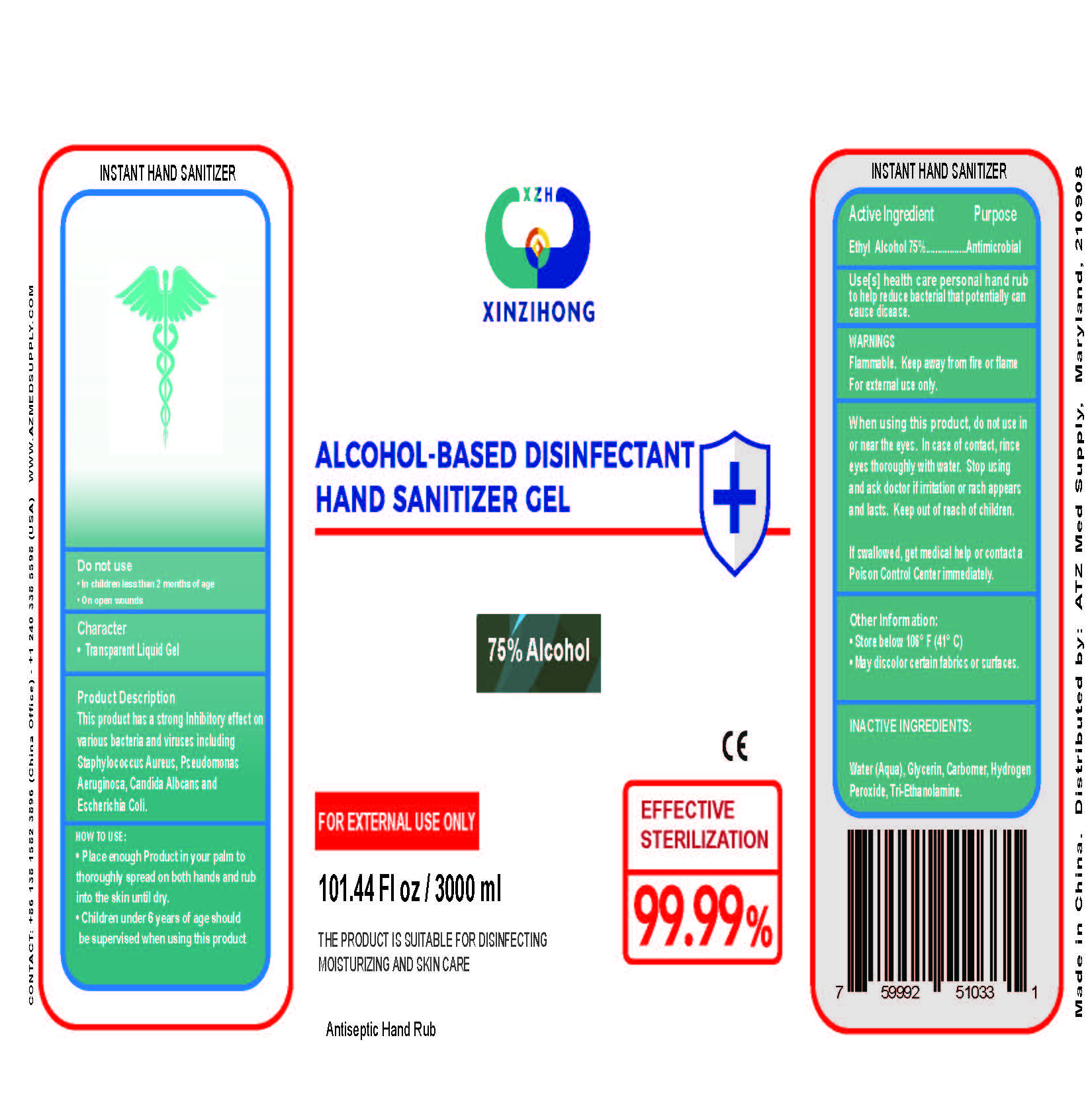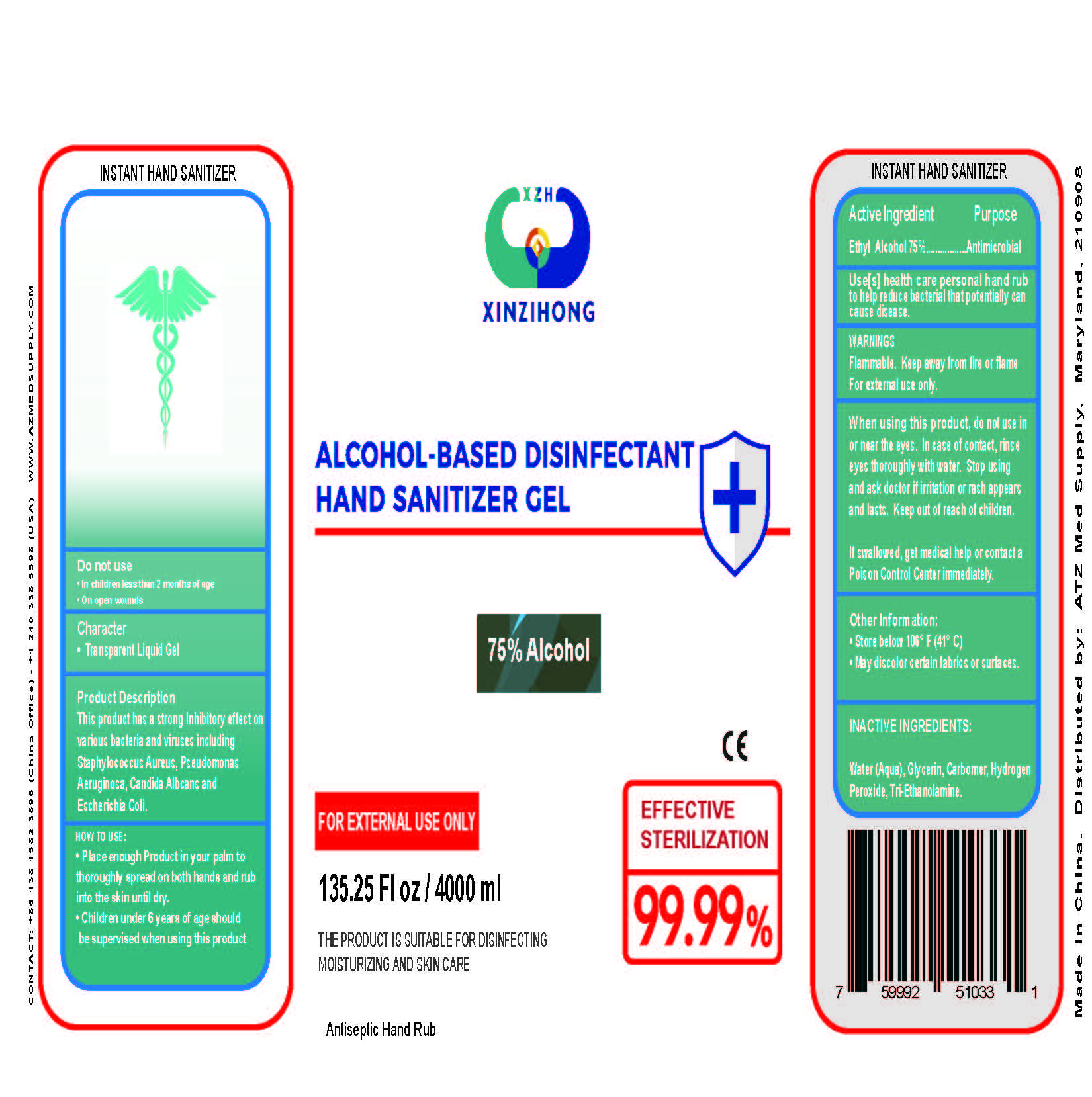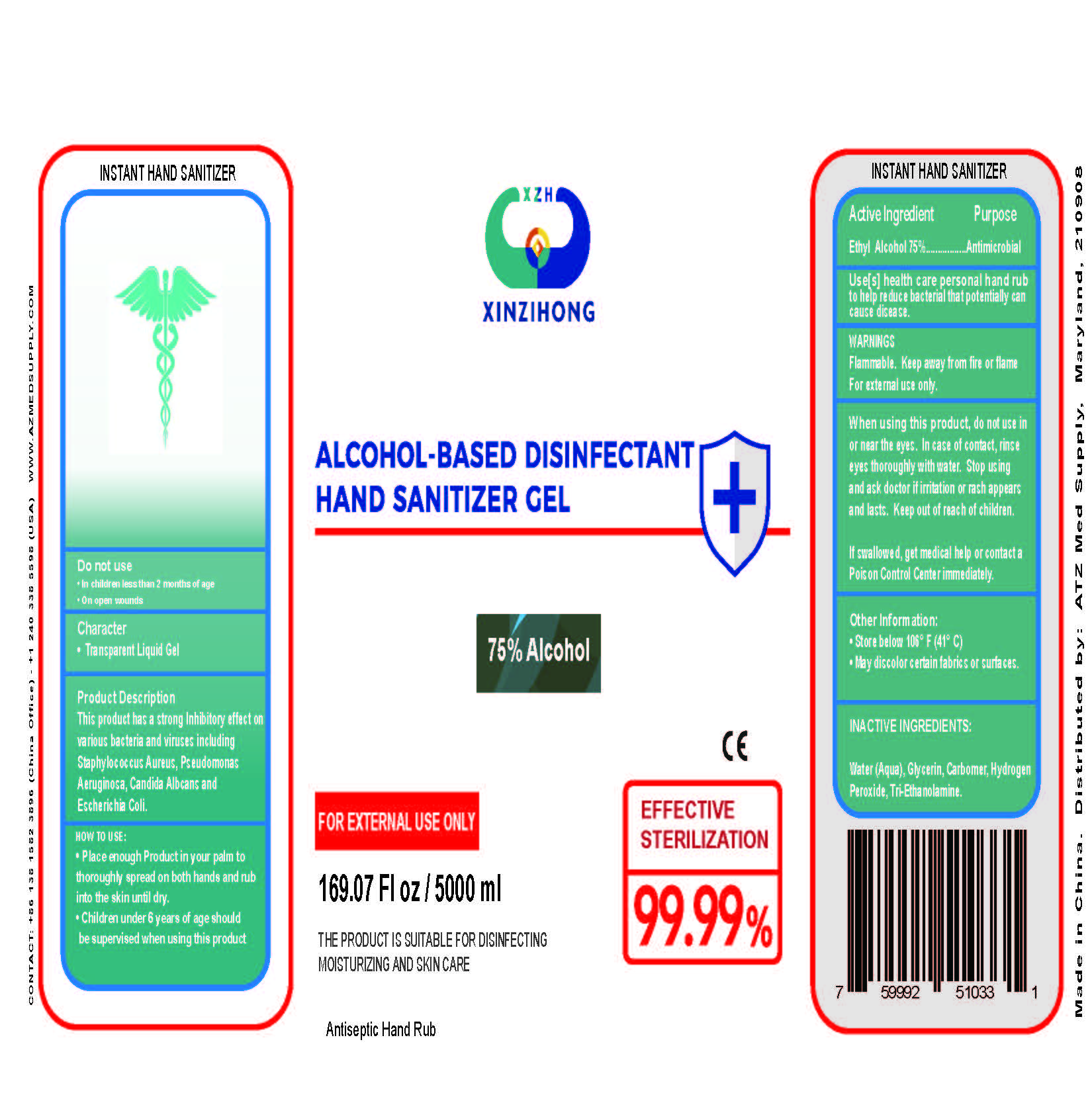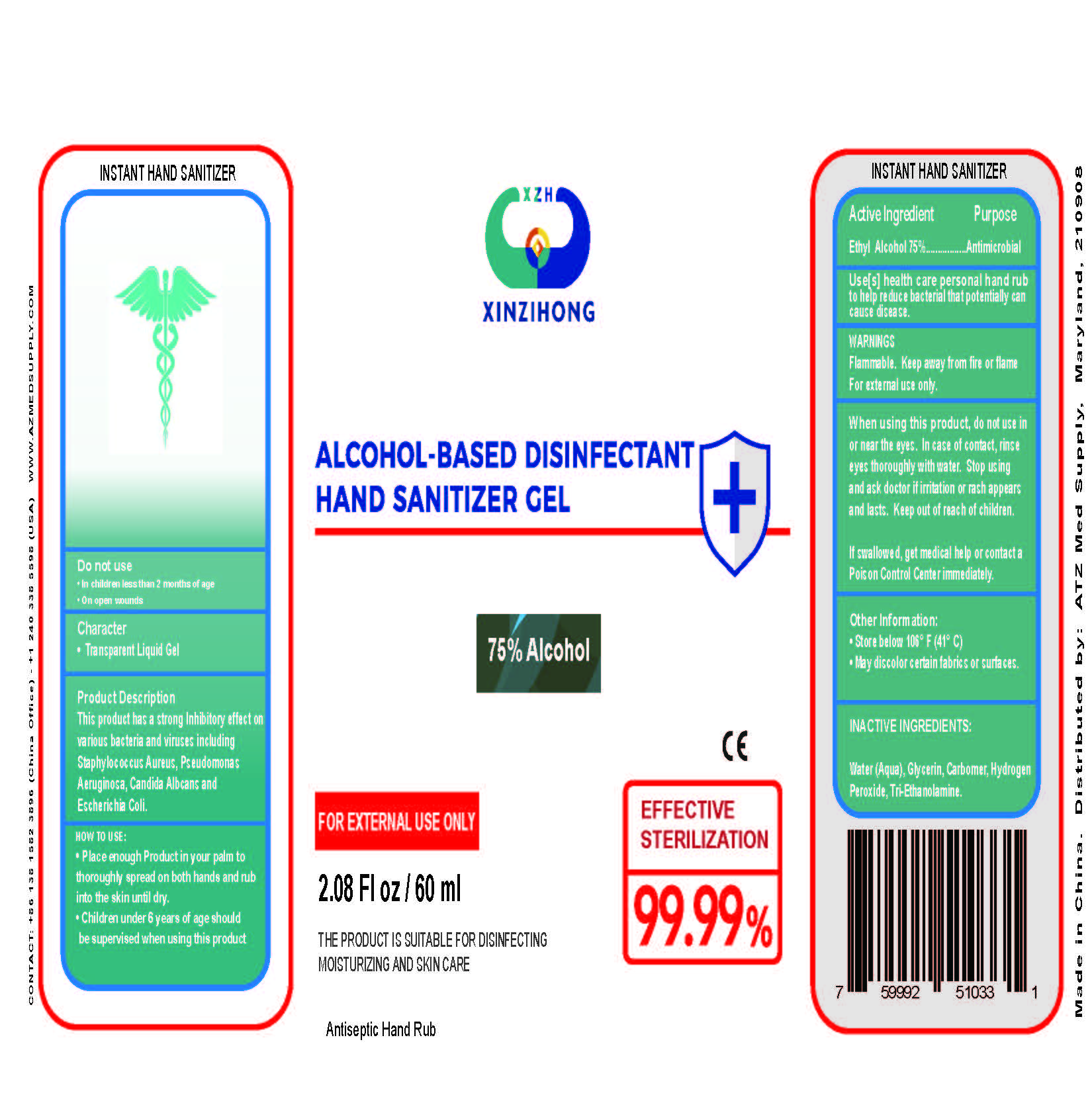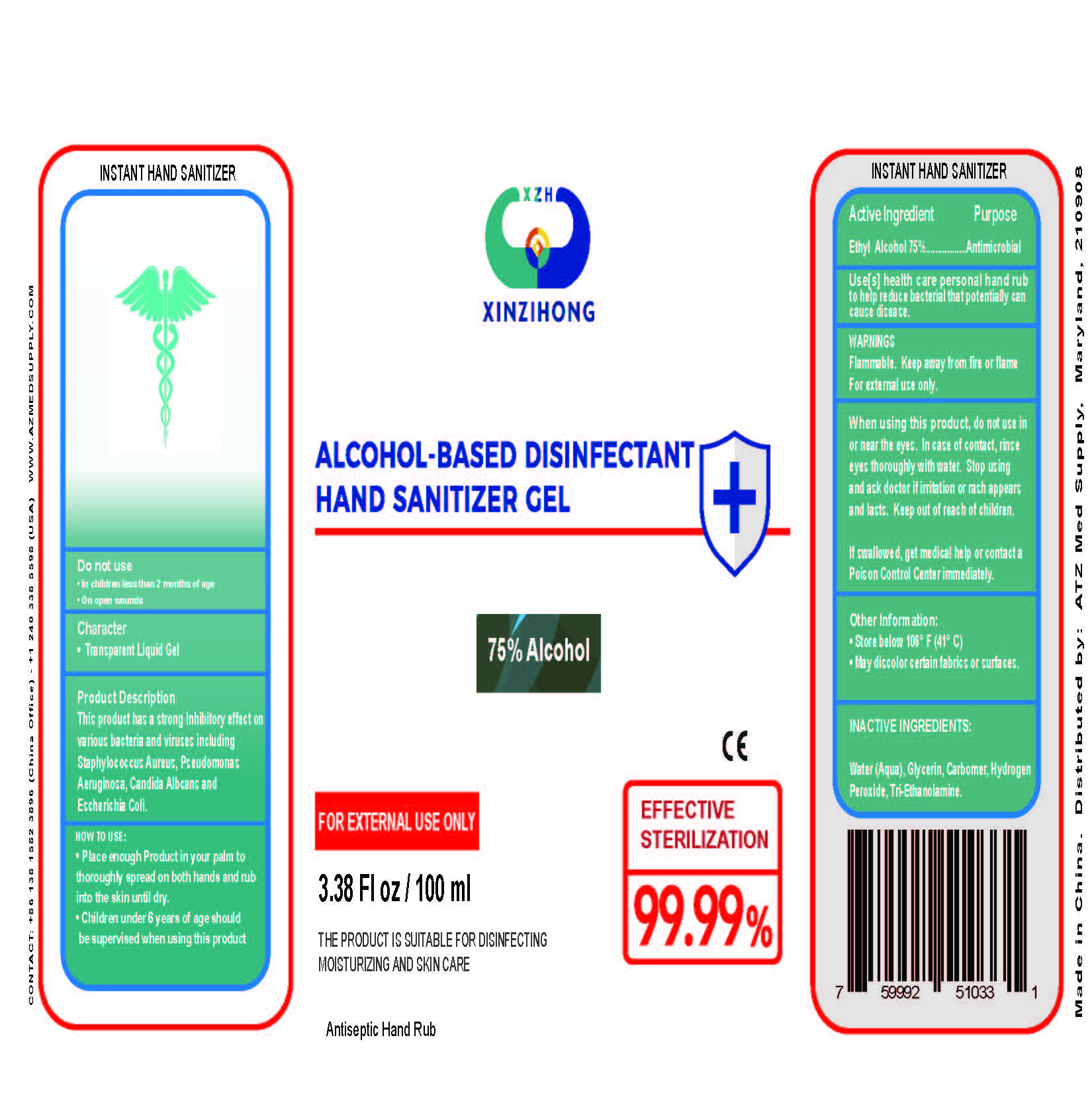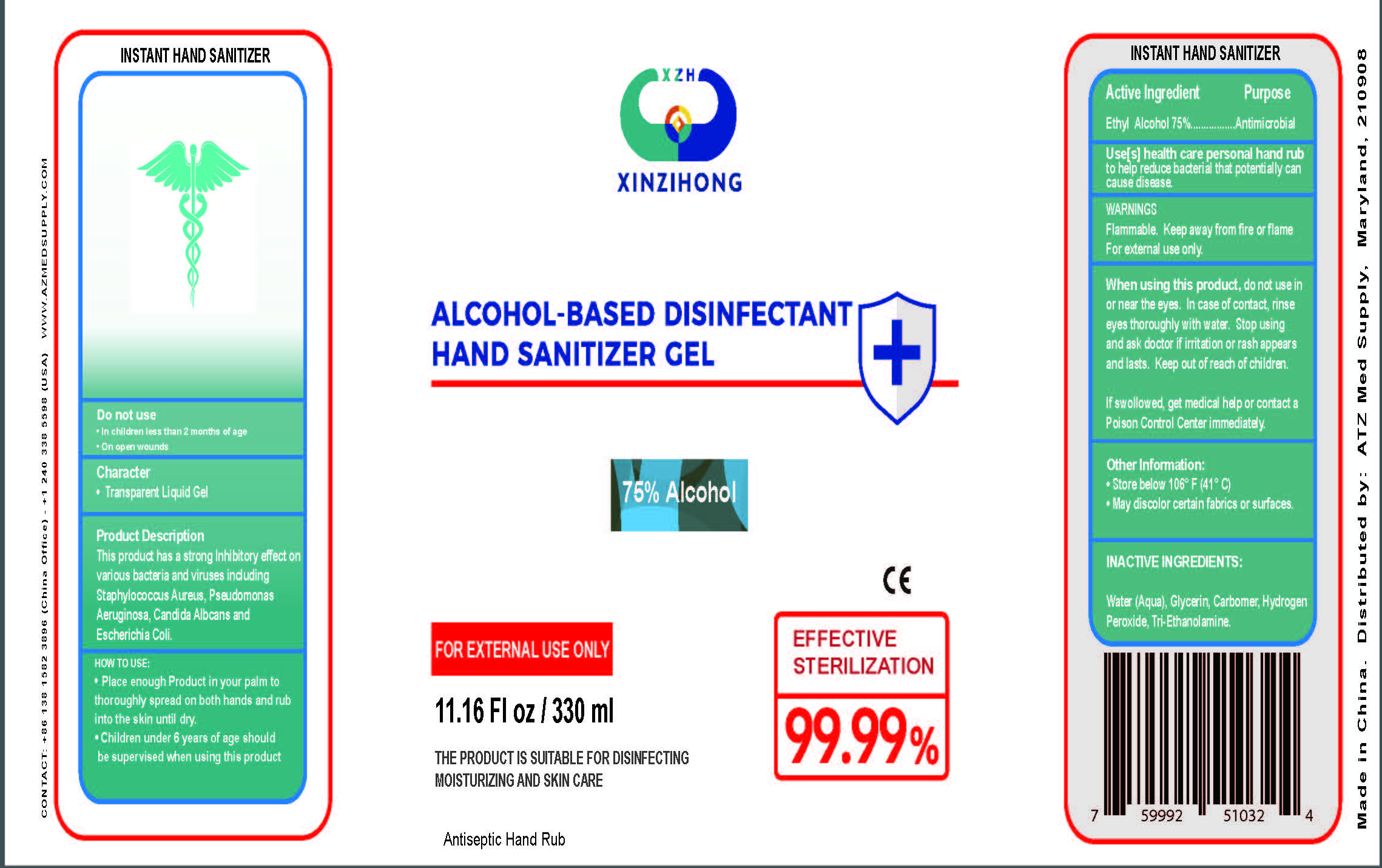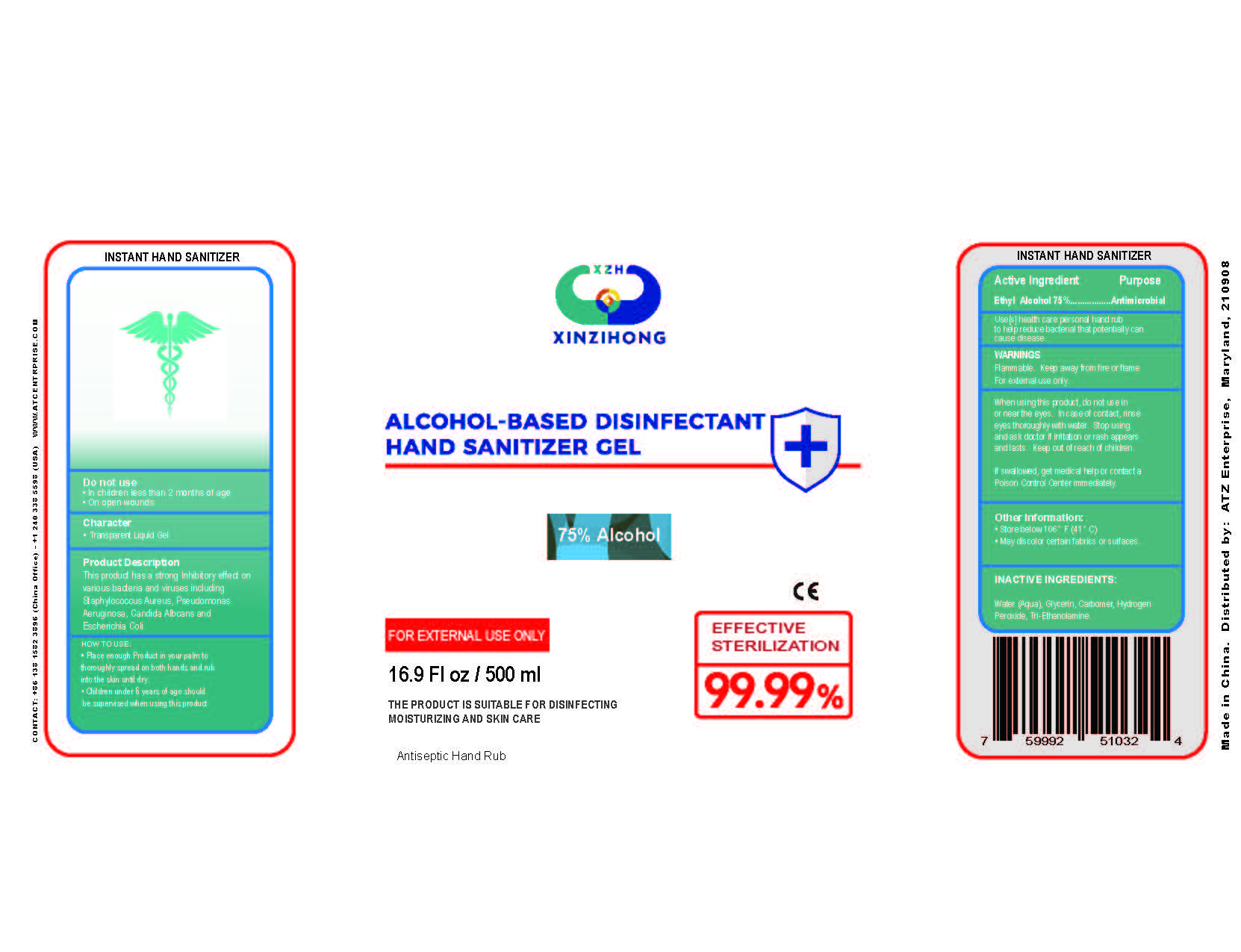 DRUG LABEL: ALCOHOL-BASED DISINFECTANT HAND SANITIZER
NDC: 74757-002 | Form: GEL
Manufacturer: GUIZHOU XINZIHONG PHARMACEUTIC ADJUVANT CO.LTD
Category: otc | Type: HUMAN OTC DRUG LABEL
Date: 20240610

ACTIVE INGREDIENTS: ALCOHOL 75 mL/100 mL
INACTIVE INGREDIENTS: CARBOMER INTERPOLYMER TYPE A (55000 CPS); TROLAMINE; GLYCERIN; HYDROGEN PEROXIDE; WATER

Active Ingredient(s)

Ethyl Alcohol 75%

Purpose

Antimicrobial

Warnings

For external use only. Flammable. Keep away from heat or flame

Do not use

- in children less than 2 months of age
- on open skin wounds

When using this product keep out of eyes, ears, and mouth. In case of contact with eyes, rinse eyes thoroughly with water.
Stop use and ask a doctor if irritation or rash occurs. These may be signs of a serious condition.
Keep out of reach of children. If swallowed, get medical help or contact a Poison Control Center right away.

STOP USE

• In children less than 2 months of age
• On open wounds

Keep out of reach of children. If swallowed, get medical help or contact a Poison Control Center right away.

Directions

- When using this product, do not use in
  or near the eyes. In case of contact, rinse
  eyes thoroughly with water. Stop using
  and ask doctor if irritation or rash appears
  and lasts. Keep out of reach of children.
  If swollowed, get medical help or contact a
  Poison Control Center immediately.

Other information

  • Store below 106° F (41° C)
  • May discolor certain fabrics or surfaces.

Inactive ingredients

glycerin, hydrogen peroxide, purified water USP

USE

• Place enough Product in your palm to thoroughly spread on both hands and rubinto the skin until dry.
• Children under 6 years of age should be supervised when using this product see full prescribing information for label